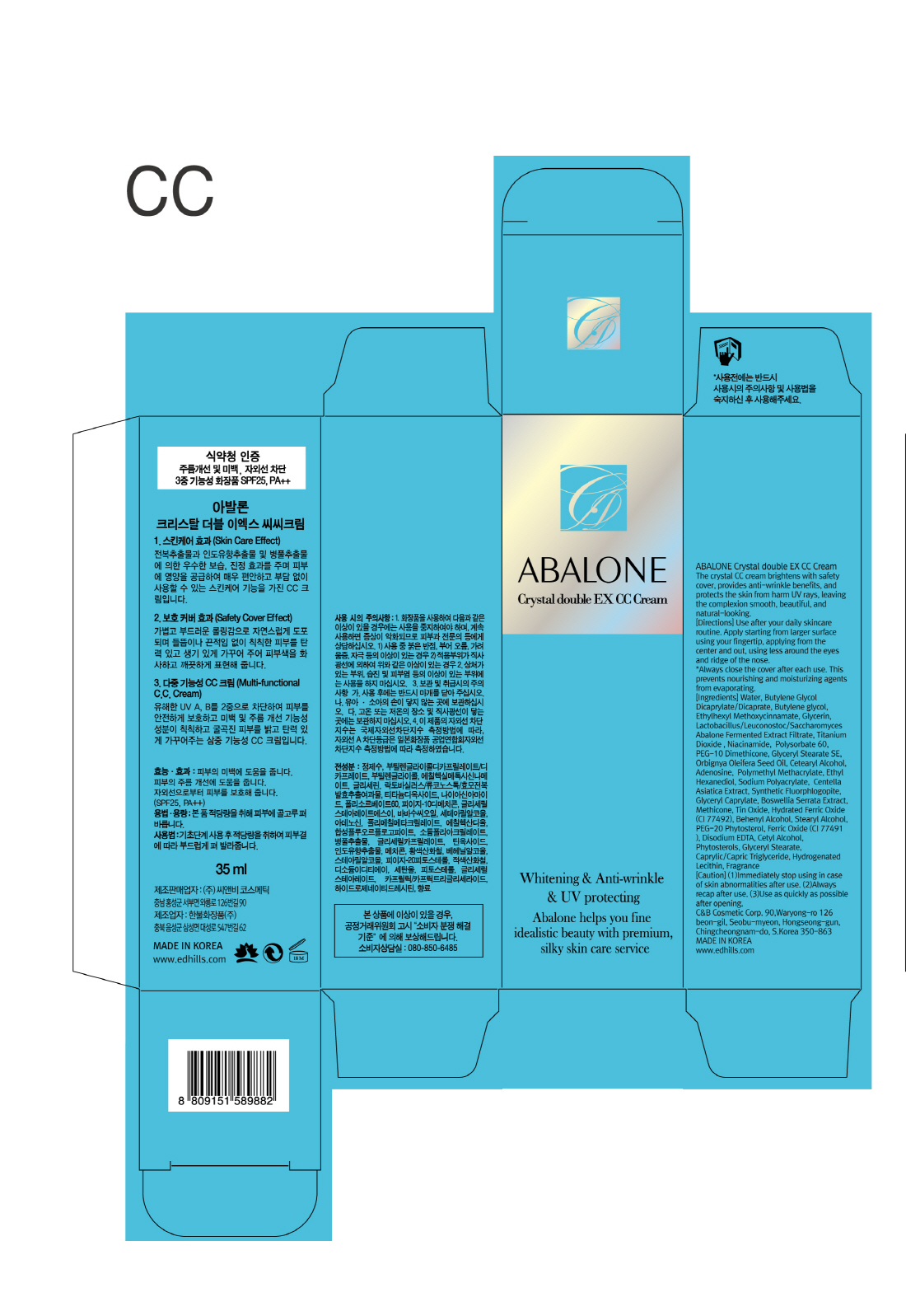 DRUG LABEL: ABALONE CRYSTALDOUBLE EX CC
NDC: 60611-0008 | Form: CREAM
Manufacturer: C&BCOSMETIC Co.,Ltd.
Category: otc | Type: HUMAN OTC DRUG LABEL
Date: 20170310

ACTIVE INGREDIENTS: NIACINAMIDE 2 g/100 mL; TITANIUM DIOXIDE 4.694 g/100 mL; ADENOSINE 0.04 g/100 mL; OCTINOXATE 7 g/100 mL
INACTIVE INGREDIENTS: WATER; GLYCERIN; BUTYLENE GLYCOL

Drug Facts

ACTIVE INGREDIENT

Niacinamide, Adenosine, Titanium Dioxide, Ethylhexyl Methoxycinnamate

INACTIVE INGREDIENT

Water, Glycerin, Butylene Glycol, Etc

PURPOSE

Skin Protectant - Anti-Wrinkle, Whitening, UV Protecting

keep out or reach of the children

INDICATIONS AND USAGE

Use after your daily skincare routine

Apply starting from larger surface using your fingertip, applying from the center and out, using less around the eyes and ridge of the nose

*Always close the cover after each use. This prevents nourishing and moisturizing agents from evaporationg.

WARNINGS

1. Do not use in the following cases(Eczema and scalp wounds)
2.Side Effects
1)Due to the use of this druf if rash, irritation, itching and symptopms of hypersnesitivity occur dicontinue use and consult your phamacisr or doctor
3.General Precautions
1)If in contact with the eyes, wash out thoroughty with water If the symptoms are servere, seek medical advice immediately
2)This product is for exeternal use only. Do not use for internal use
4.Storage and handling precautions
1)If possible, avoid direct sunlight and store in cool and area of low humidity
2)In order to maintain the quality of the product and avoid misuse
3)Avoid placing the product near fire and store out in reach of children

DOSAGE AND ADMINISTRATION

for external use only